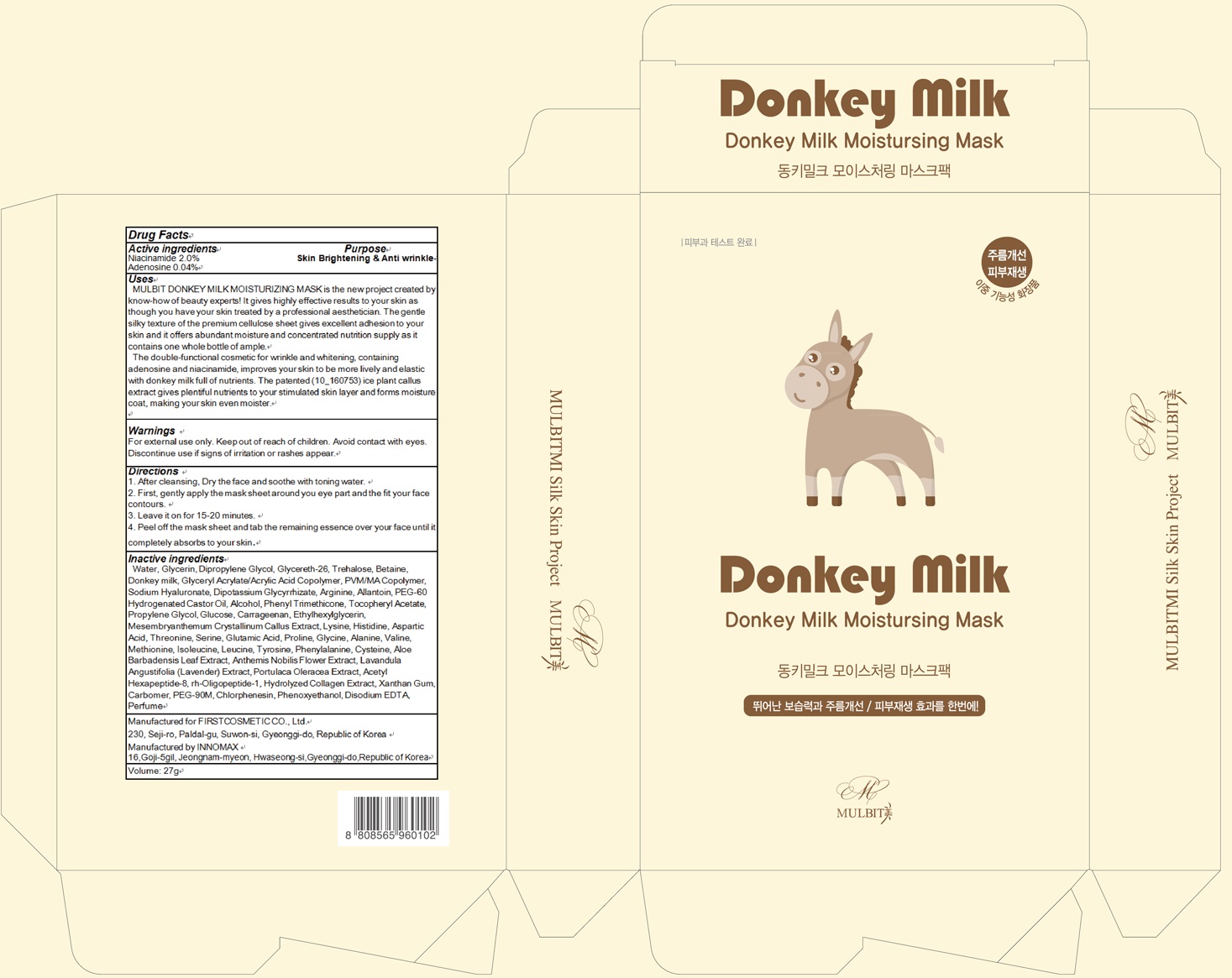 DRUG LABEL: MULBIT Donkey Milk Mask
NDC: 71635-050 | Form: PATCH
Manufacturer: First Cosmetic Co., Ltd
Category: otc | Type: HUMAN OTC DRUG LABEL
Date: 20171020

ACTIVE INGREDIENTS: Niacinamide 0.54 g/27 g; Adenosine 0.01 g/27 g
INACTIVE INGREDIENTS: Water; Glycerin

ACTIVE INGREDIENT

Active ingredients: Niacinamide 2.0%, Adenosine 0.04%

INACTIVE INGREDIENT

Inactive ingredients: Water, Glycerin, Dipropylene Glycol, Glycereth-26, Trehalose, Betaine, Donkey milk, Glyceryl Acrylate/Acrylic Acid Copolymer, PVM/MA Copolymer, Sodium Hyaluronate, Dipotassium Glycyrrhizate, Arginine, Allantoin, PEG-60 Hydrogenated Castor Oil, Alcohol, Phenyl Trimethicone, Tocopheryl Acetate, Propylene Glycol, Glucose, Carrageenan, Ethylhexylglycerin, Mesembryanthemum Crystallinum Callus Extract, Lysine, Histidine, Aspartic Acid, Threonine, Serine, Glutamic Acid, Proline, Glycine, Alanine, Valine, Methionine, Isoleucine, Leucine, Tyrosine, Phenylalanine, Cysteine, Aloe Barbadensis Leaf Extract, Anthemis Nobilis Flower Extract, Lavandula Angustifolia (Lavender) Extract, Portulaca Oleracea Extract, Acetyl Hexapeptide-8, rh-Oligopeptide-1, Hydrolyzed Collagen Extract, Xanthan Gum, Carbomer, PEG-90M, Chlorphenesin, Phenoxyethanol, Disodium EDTA, Perfume

PURPOSE

Purpose: Skin Brightening & Anti wrinkle

WARNINGS

Warnings: For external use only. Keep out of reach of children. Avoid contact with eyes. Discontinue use if signs of irritation or rashes appear.

KEEP OUT OF REACH OF CHILDREN

Uses

Uses: MULBIT DONKEY MILK MOISTURIZING MASK is the new project created by know-how of beauty experts! It gives highly effective results to your skin as though you have your skin treated by a professional aesthetician. The gentle silky texture of the premium cellulose sheet gives excellent adhesion to your skin and it offers abundant moisture and concentrated nutrition supply as it contains one whole bottle of ample. The double-functional cosmetic for wrinkle and whitening, containing adenosine and niacinamide, improves your skin to be more lively and elastic with donkey milk full of nutrients. The patented (10_160753) ice plant callus extract gives plentiful nutrients to your stimulated skin layer and forms moisture coat, making your skin even moister.

Directions

Directions: 1. After cleansing, Dry the face and soothe with toning water. 2. First, gently apply the mask sheet around you eye part and the fit your face contours. 3. Leave it on for 15-20 minutes. 4. Peel off the mask sheet and tab the remaining essence over your face until it completely absorbs to your skin.